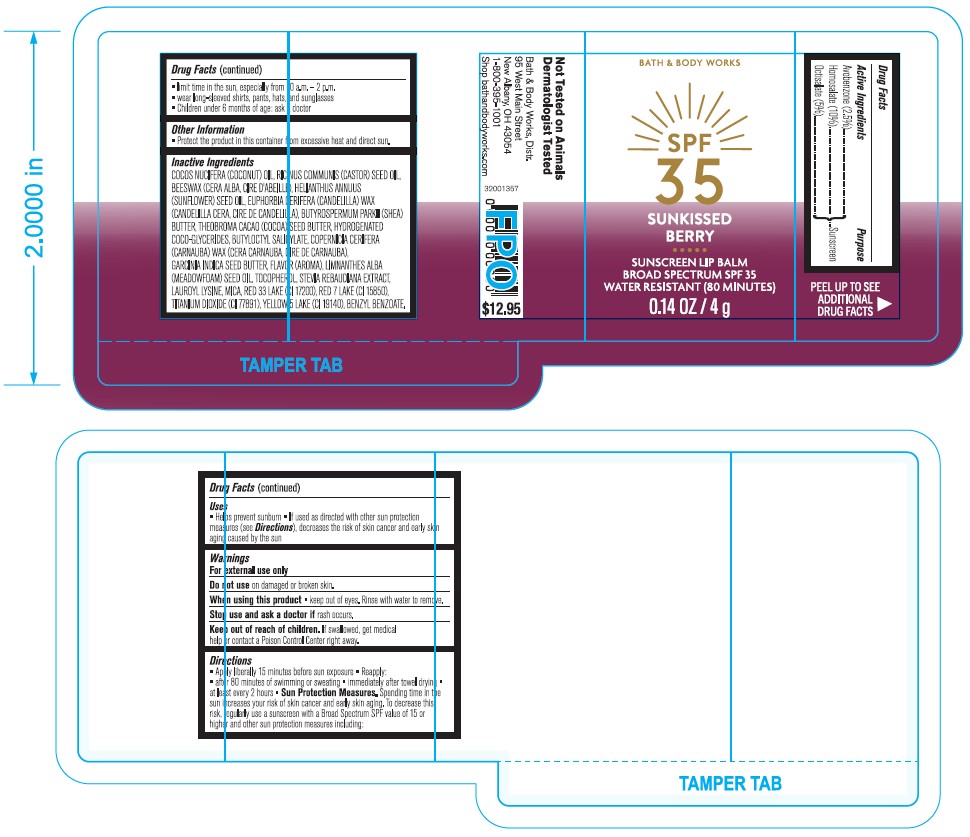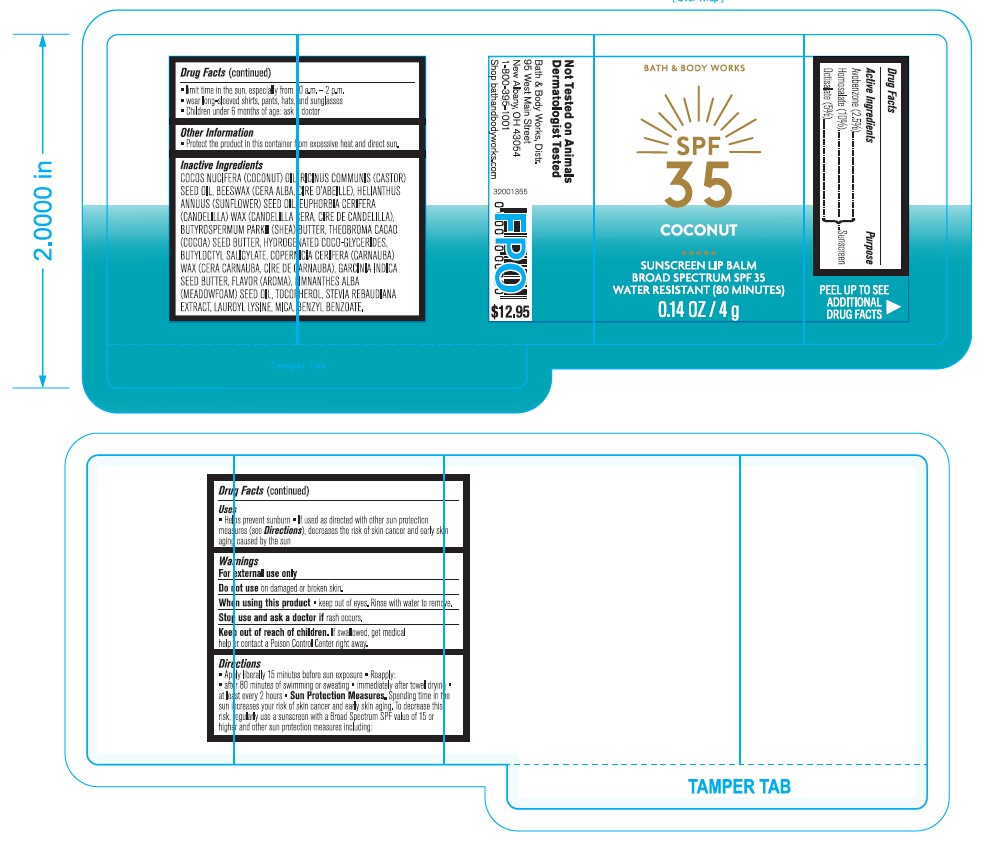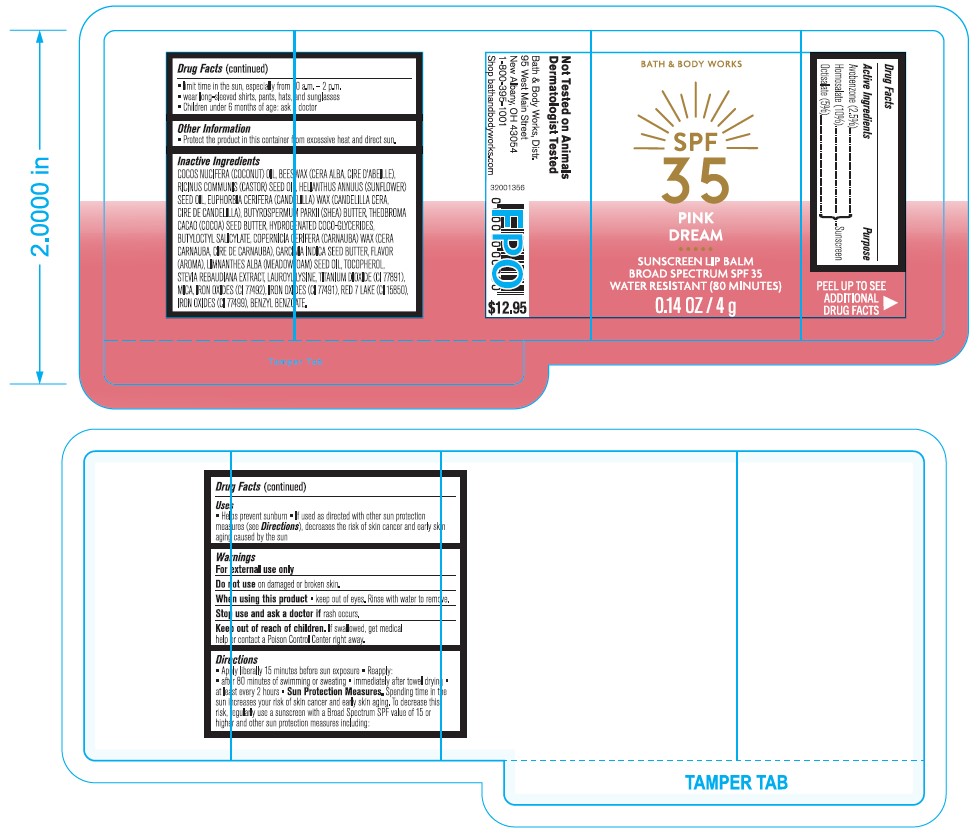 DRUG LABEL: Bath and Body Works SPF 35 Summer Crush Lip Balm
NDC: 62670-6609 | Form: STICK
Manufacturer: Bath and Body Works, Inc.
Category: otc | Type: HUMAN OTC DRUG LABEL
Date: 20240122

ACTIVE INGREDIENTS: HOMOSALATE 10 g/100 g; OCTISALATE 5 g/100 g; AVOBENZONE 2.5 g/100 g
INACTIVE INGREDIENTS: FERRIC OXIDE YELLOW; FERRIC OXIDE RED; FERROSOFERRIC OXIDE; MEADOWFOAM SEED OIL; MICA; .ALPHA.-TOCOPHEROL, DL-; SOYBEAN OIL; BENZYL BENZOATE; BENZYL SALICYLATE; TITANIUM DIOXIDE; D&C RED NO. 7; GARCINIA INDICA SEED BUTTER; STEVIA REBAUDIUNA LEAF; SHEA BUTTER; BENZYL ALCOHOL; ANISE OIL; SUNFLOWER OIL; LAUROYL LYSINE; COCOA BUTTER; HYDROGENATED COCO-GLYCERIDES; BUTYLOCTYL SALICYLATE; COCONUT OIL; CANDELILLA WAX; CASTOR OIL; YELLOW WAX; CARNAUBA WAX

ACTIVE INGREDIENT

Avobenzone - 2.5%

Octisalate - 5%

Homosalate - 10%

PURPOSE

Avobenzone - Sunscreen

Octisalate - Sunscreen

Homosalate - Sunscreen

DOSAGE AND ADMINISTRATION

Apply liberally 15 minutes before sun exposire. Reapply:

- after 80 minutes of swimming or sweating
- immediately after towel drying
- at least every 2 hours

WARNINGS

For external use only

Do not use on damaged or broken skin

When using this product, keep out of eyes. Rinse with water to remove

Stop use and ask a doctor if rash occurs

INSTRUCTIONS FOR USE

Limit time in the sun, especially from 10am-2pm

Wear long sleeved shirts, pants, hats and sunglasses

Childresn under 6 months of age, ask doctor

OTHER SAFETY INFORMATION

Protect the product in this container from excessive heat and direct sun

INACTIVE INGREDIENT

Natural Inactive Ingredients: Cocos Nucifera (Coconut) Oil, Ricinus Communis (Castor) Seed Oil, Beeswax, Helianthus Annuus (Sunflower) Seed Oil, Euphorbia Cerifera (Candelilla) Wax, Butyrospermum Parkii (Shea) Butter, Theobroma Cacao (Cocoa) Seed Butter, Butyloctyl Salicylate, Hydrogenated Coco-Glycerides, Copernicia Cerifera (Carnauba) Wax, Garcinia Indica Seed Butter, Flavor, Limnanthes Alba (Meadowfoam) Seed Oil, Benzyl Benzoate, Mica, Tocopherol, Stevia Rebaudiana Leaf/Stem Extract, Lauroyl Lysine, Glycine Soja (Soybean) Oil, Benzyl Alcohol, Benzyl Salicylate.

Berry Inactive Ingredients: Cocos Nucifera (Coconut) Oil, Ricinus Communis (Castor) Seed Oil, Beeswax, Helianthus Annuus (Sunflower) Seed Oil, Euphorbia Cerifera (Candelilla) Wax, Butyrospermum Parkii (Shea) Butter, Theobroma Cacao (Cocoa) Seed Butter, Butyloctyl Salicylate, Hydrogenated Coco-Glycerides, Copernicia Cerifera (Carnauba) Wax, Garcinia Indica Seed Butter, Flavor, Limnanthes Alba (Meadowfoam) Seed Oil, Benzyl Benzoate, Mica, Red 33 Lake (CI 17200), Red 7 Lake (CI 15850), Titanium Dioxide (CI 77891), Yellow 5 Lake (CI 19140), Tocopherol, Stevia Rebaudiana Leaf/Stem Extract, Lauroyl Lysine, Glycine Soja (Soybean) Oil, Benzyl Alcohol, Benzyl Salicylate.

Summer Crush Inactive Ingredients: Cocos Nucifera (Coconut) Oil, Beeswax, Ricinus Communis (Castor) Seed Oil, Helianthus Annuus (Sunflower) Seed Oil, Euphorbia Cerifera (Candelilla) Wax, Butyrospermum Parkii (Shea) Butter, Theobroma Cacao (Cocoa) Seed Butter, Butyloctyl Salicylate, Hydrogenated Coco-Glycerides, Copernicia Cerifera (Carnauba) Wax, Garcinia Indica Seed Butter, Titanium Dioxide (CI 77891), Flavor, Limnanthes Alba (Meadowfoam) Seed Oil, Benzyl Benzoate, Mica, Iron Oxide (CI 77492), Iron Oxides (CI 77491), Red 7 Lake (CI 15850), Tocopherol, Iron Oxides (CI77499), Stevia Rebaudiana Leaf/Stem Extract, Lauroyl Lysine, Glycine Soja (Soybean) Oil, Benzyl Alcohol, Benzyl Salicylate.

QUESTIONS

1-800-395-1001

INDICATIONS AND USAGE

Helps prevent sunburn if used as directed with other sun protection measures (see Directions), decreases the risk of skin cancer and early aging caused by the sun

Keep out of reach of children. If swallowed, get medical help or contact a Poison Control Center right away